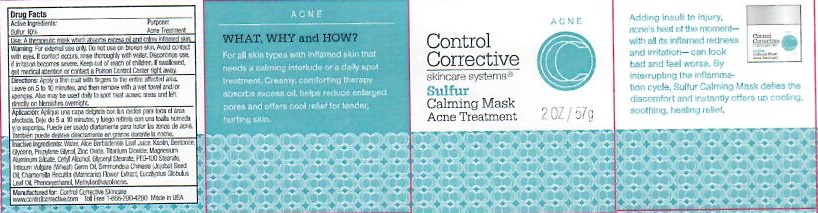 DRUG LABEL: SULFUR CALMING MASK
NDC: 70764-103 | Form: CREAM
Manufacturer: CONTROL CORRECTIVE SKINCARE INC
Category: otc | Type: HUMAN OTC DRUG LABEL
Date: 20251231

ACTIVE INGREDIENTS: SULFUR 10 g/100 g
INACTIVE INGREDIENTS: WATER; ALOE VERA LEAF; KAOLIN; BENTONITE; GLYCERIN; PROPYLENE GLYCOL; ZINC OXIDE; TITANIUM DIOXIDE; MAGNESIUM ALUMINUM SILICATE; CETYL ALCOHOL; GLYCERYL MONOSTEARATE; PEG-100 STEARATE; WHEAT GERM OIL; JOJOBA OIL; MATRICARIA CHAMOMILLA FLOWERING TOP; EUCALYPTUS OIL; PHENOXYETHANOL; METHYLISOTHIAZOLINONE

CONTROL CORRECTIVE - SULFUR CALMING MASK (70764-103)

ACTIVE INGREDIENTS

SULFUR 10%

PURPOSE

ACNE TREATMENT

USE

A THERAPEUTIC MASK WHICH ABSORBS EXCESS OIL AND CALMS INFLAMMED SKIN.

WARNINGS

FOR EXTERNAL USE ONLY. DO NOT USE ON BROKEN SKIN. AVOID CONTACT WITH EYES. IF CONTACT OCCURS, RINSE THOROUGHLY WITH WATER. DISCONTINUE USE IF IRRITATION BECOMES SEVERE.

KEEP OUT OF REACH OF CHILDREN. IF SWALLOWED, GET MEDICAL ATTENTION OR CONTACT A POISON CONTROL CENTER RIGHT AWAY.

DIRECTIONS

Apply a thin layer with fingers to the entire affected areas. Leave on 5 to 10 minutes and then remove with a wet towel or sponge. Also may be used daily to spot treat acneic areas or left directly on blemishes overnight.

INACTIVE INGREDIENTS

WATER, ALOE BARBADENSIS LEAF JUICE, KAOLIN, BENTONITE, GLYCERIN, PROPYLENE GLYCOL, ZINC OXIDE, TITANIUM DIOXIDE, MAGNESIUM ALUMINUM SILICATE, CETYL ALCOHOL, GLYCERYL STEARATE, PEG-100 STEARATE, TRITICUM VULGARE (WHEAT) GERM OIL, SIMMONDSIA CHINENIS (JOJOBA) SEED OIL, CHAMOMILE RECUTITA (MATRICARIA) FLOWER EXTRACT, EUCALYPTUS GLOBULUS LEAF OIL, PHENOXYETHANOL, METHYLISOTHIAZOLINONE.

QUESTIONS OR COMMENTS

WWW.CONTROLCORRECTIVE.COM

TOLL FREE 1-866-290-4290 MADE IN USA